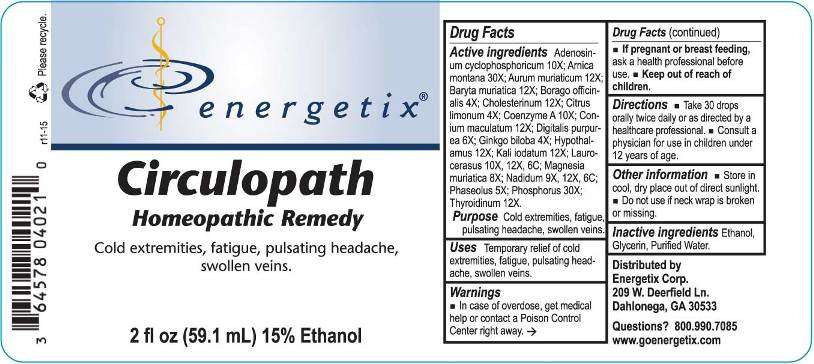 DRUG LABEL: Circulopath
NDC: 64578-0118 | Form: LIQUID
Manufacturer: Energetix Corp
Category: homeopathic | Type: HUMAN OTC DRUG LABEL
Date: 20160217

ACTIVE INGREDIENTS: ADENOSINE CYCLIC PHOSPHATE 10 [hp_X]/1 mL; ARNICA MONTANA 30 [hp_X]/1 mL; GOLD TRICHLORIDE 12 [hp_X]/1 mL; BARIUM CHLORIDE DIHYDRATE 12 [hp_X]/1 mL; BORAGE 4 [hp_X]/1 mL; CHOLESTEROL 12 [hp_X]/1 mL; LEMON JUICE 4 [hp_X]/1 mL; COENZYME A 10 [hp_X]/1 mL; CONIUM MACULATUM FLOWERING TOP 12 [hp_X]/1 mL; DIGITALIS 6 [hp_X]/1 mL; GINKGO 4 [hp_X]/1 mL; BOS TAURUS HYPOTHALAMUS 12 [hp_X]/1 mL; POTASSIUM IODIDE 12 [hp_X]/1 mL; PRUNUS LAUROCERASUS LEAF 10 [hp_X]/1 mL; MAGNESIUM CHLORIDE 8 [hp_X]/1 mL; NADIDE 9 [hp_X]/1 mL; KIDNEY BEAN 5 [hp_X]/1 mL; PHOSPHORUS 30 [hp_X]/1 mL; THYROID, BOVINE 12 [hp_X]/1 mL
INACTIVE INGREDIENTS: WATER; GLYCERIN; ALCOHOL

Drug Facts:

ACTIVE INGREDIENTS:

Adenosinum cyclophosphoricum 10X; Arnica montana 30X; Aurum muriaticum 12X; Baryta muriatica 12X; Borago officinalis 4X; Cholesterinum 12X; Citrus limonum 4X; Hypothalamus (Bovine) 12X; Kali iodatum 12X; Laurocerasus 10X, 12X, 6C; Magnesia muriatica 8X, Nadidum 9X, 12X, 6C; Phaseolus 5X; Phosphorus 30X; Thyroidinum (Bovine) 12X.

PURPOSE:

Cold extremities, fatigue, pulsating headache, swollen veins.

WARNINGS:

In case of overdose, get medical help or contact a Poison Control Center right away.
If pregnant or breast feeding, ask a health professional before use.
Keep out of reach of children.

Other information
Store in a cool, dry place out of direct sunlight.
Do not use if neck wrap is broken or missing.

Keep out of reach of children. In case of overdose, get medical help or contact a Poison Control Center right away.

DIRECTIONS:

Take 30 drops orally twice daily or as directed by a healthcare professional.
Consult a physician for use in children under 12 years of age.

USES:

Temporary relief of cold extremities, fatigue, pulsating headache, swollen veins.

INACTIVE INGREDIENTS:

Purified Water, Glycerin 15%, Ethanol 15%.

QUESTIONS:

Distributed by
Energetix Corp.
Dahlonega, GA 30533

Questions? 800.990.7085
www.goenergetix.com

PACKAGE LABEL DISPLAY:

energetix
Circulopath
Homeopathic Remedy

Cold extremities, fatigue, pulsating headache,

swollen veins.

2 fl oz (59.1 mL)